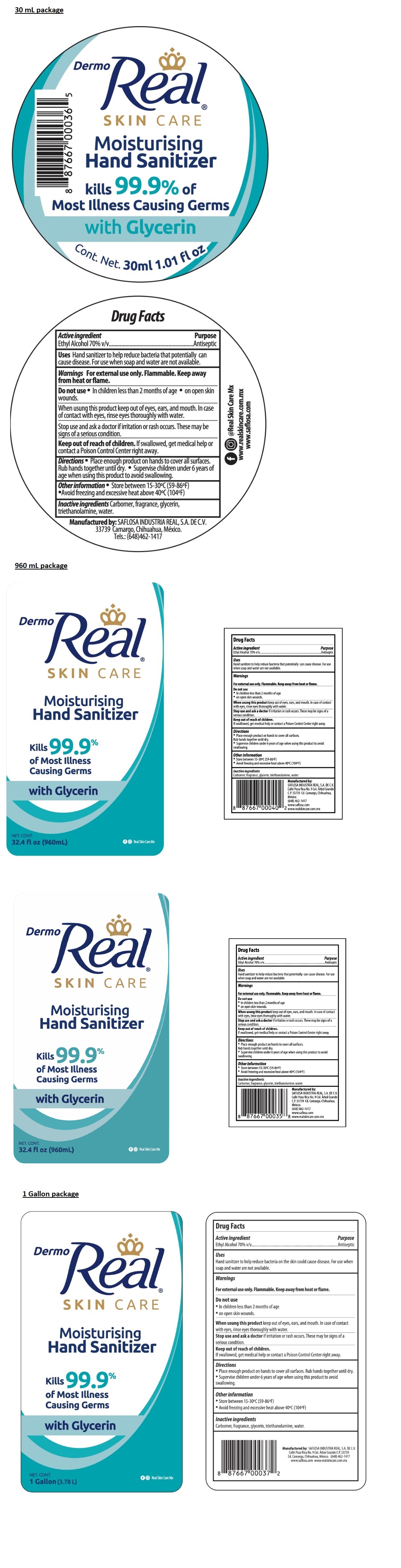 DRUG LABEL: Dermo Real
NDC: 78009-110 | Form: GEL
Manufacturer: Saflosa Industria Real, S.A. de C.V.
Category: otc | Type: HUMAN OTC DRUG LABEL
Date: 20200520

ACTIVE INGREDIENTS: ALCOHOL 70 mL/100 mL
INACTIVE INGREDIENTS: CARBOMER HOMOPOLYMER, UNSPECIFIED TYPE; GLYCERIN; TROLAMINE; WATER

Dermo Real® SKIN CARE Moisturising Hand Sanitizer

Active ingredient

Ethyl Alcohol 70% v/v

Purpose

Antiseptic

Uses

Hand sanitizer to help reduce bacteria that potentially can cause disease. For use when soap and water are not available.

Warnings

For external use only. Flammable. Keep away from heat or flame.

Do not use

- In children less than 2 months of age
- on open skin wounds.

When using this product keep out of eyes, ears, and mouth. In case of contact with eyes, rinse eyes thoroughly with water.

Stop use and ask a doctor if irritation or rash occurs. These may be signs of a serious condition.

Keep out of reach of children.

If swallowed, get medical help or contact a Poison Control Center right away.

Directions

- Place enough product on hands to cover all surfaces. Rub hands together until dry.
- Supervise children under 6 years of age when using this product to avoid swallowing.

Other information

- Store between 15-30ºC (59-86ºF)
- Avoid freezing and excessive heat above 40ºC (104ºF)

Inactive ingredients

Carbomer, fragrance, glycerin, triethanolamine, water.

Kills 99.9% of Most Illness Causing Germs

with Glycerin

@Real Skin Care Mx

Manufactured by:

SAFLOSA INDUSTRIA REAL, S.A. DE C.V.
Calle Poza Rica No. 9 Col. Arbol Grande C.P. 33739
Cd. Camargo, Chihuahua, México.

Tels.: (648) 462-1417
www.saflosa.com

www.realskincare.com.mx